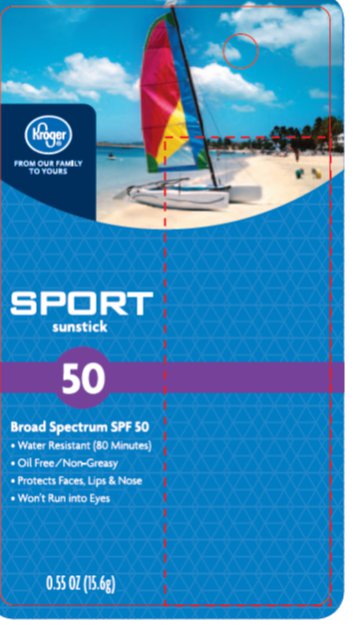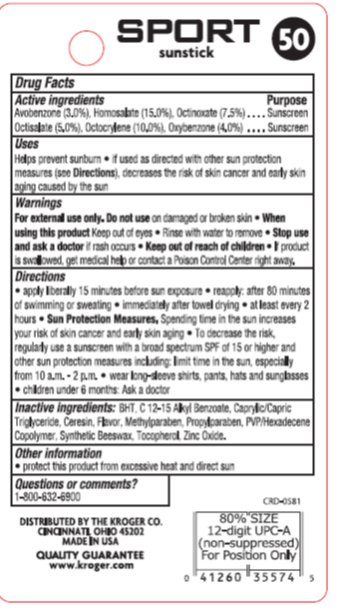 DRUG LABEL: Kroger Sport SPF 50 Sunstick
NDC: 30142-933 | Form: STICK
Manufacturer: Kroger
Category: otc | Type: HUMAN OTC DRUG LABEL
Date: 20130430

ACTIVE INGREDIENTS: AVOBENZONE 3.00 mg/1 g; HOMOSALATE 15 mg/1 g; OCTINOXATE 7.5 mg/1 g; OCTISALATE 5.00 mg/1 g; OCTOCRYLENE 10 mg/1 g; OXYBENZONE 4.00 mg/1 g
INACTIVE INGREDIENTS: CERESIN 15.00 mg/1 g; WHITE WAX 14.5 mg/1 g; MEDIUM-CHAIN TRIGLYCERIDES 10.00 mg/1 g; ZINC OXIDE 6.00 mg/1 g; ALKYL (C12-15) BENZOATE 5.00 mg/1 g

Drug Facts

Active ingredient

Avobenzone, Homosalate, Octinoxate, Octisalate, Octocrylene, Oxybenzone

Purpose

Sunscreen, Sunscreen, Sunscreen, Sunscreen, Sunscreen, Sunscreen,

Keep Out of Reach of Children

If product is swallowed, get medical help or contact a Poison Control Center right away.

Uses

Helps prevent sunburn. If used as directed with other sun protection measures (see Directions), decreases the risk of skin cancer and early skin aging caused by the sun.

Warnings

For external use only. Do not use on damaged or broken skin. When using this product keep out of eyes. Rinse with water to remove. Stop use and ask a doctor if rash occurs.

Directions

Apply liberally 15 minutes before sun exposure. Reapply after 80 minutes of swimming or sweating. immediately after towel drying. at least every two hours. Sun Protection Measures: Spending time in the sun increases your risk of skin cancer and early skin aging. To decrease the risk, regularly use a sunscreen with a broad spectrum SPF of 15 or higher and other sun protection measures including: limit time in the sun, especially from 10 a.m. – 2 p.m. Wear long-sleeve shirts, pants, hats and sunglasses. Children under 6 months of age; Ask a doctor.

Inactive Ingredients

BHT, C 12- 15 Alkyl Benzoat, Caprylic/Capric Triglyceride, Ceresin, Flavor, Methylparaben, Propylparaben, PVP/Hexadecene Copolymer, Synthetic Beeswax, Tocopherol, Zinc Oxide.